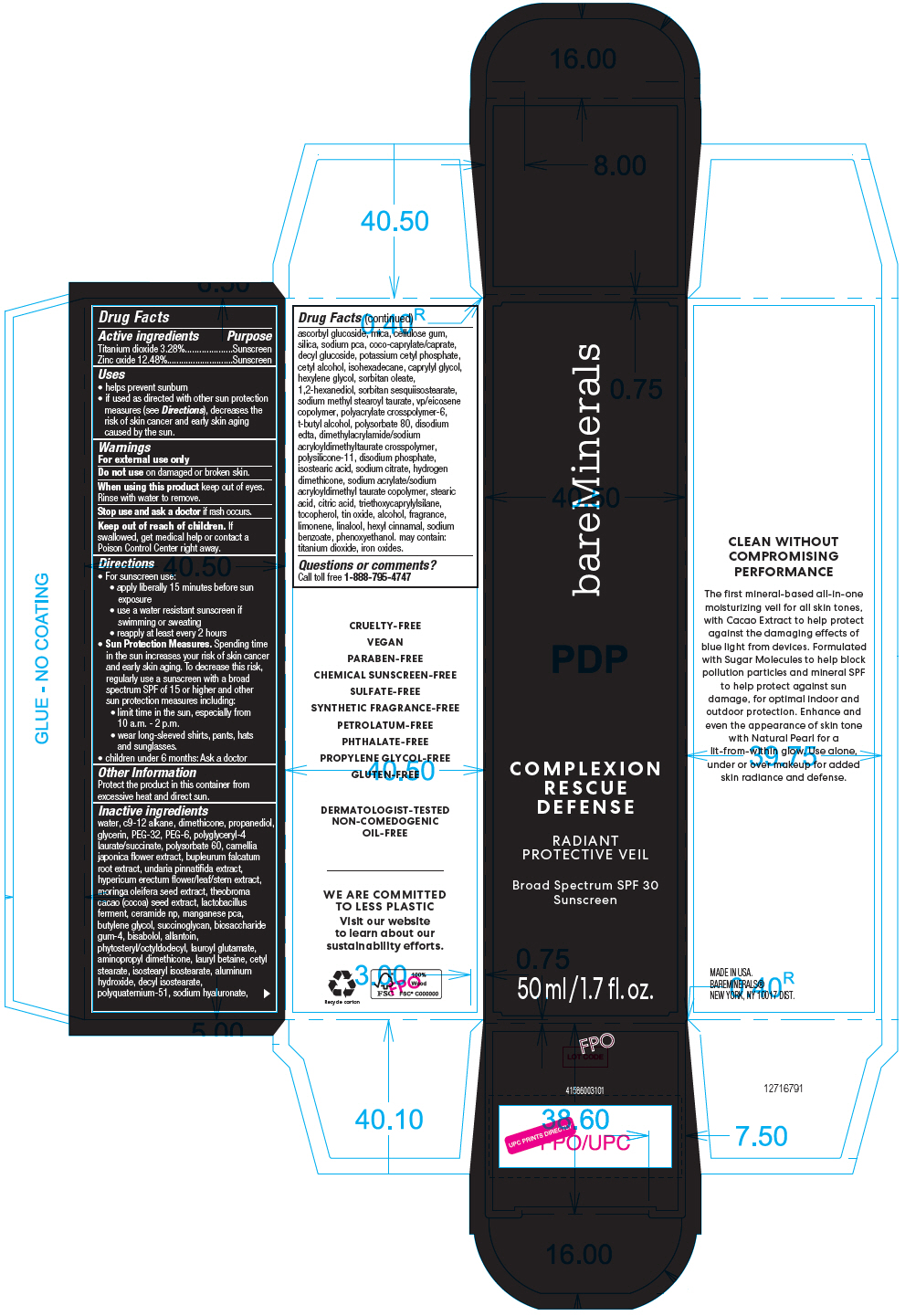 DRUG LABEL: bareMinerals Complexion Rescue Defense Radiant Protective Veil Broad Spectrum SPF 30
NDC: 98132-000 | Form: CREAM
Manufacturer: Orveon Global US LLC
Category: otc | Type: HUMAN OTC DRUG LABEL
Date: 20231004

ACTIVE INGREDIENTS: TITANIUM DIOXIDE 32.8 mg/1 mL; ZINC OXIDE 124.8 mg/1 mL
INACTIVE INGREDIENTS: WATER; DIMETHICONE; PROPANEDIOL; GLYCERIN; POLYETHYLENE GLYCOL 1600; POLYETHYLENE GLYCOL 300; POLYSORBATE 60; CAMELLIA JAPONICA FLOWER; BUPLEURUM FALCATUM ROOT; UNDARIA PINNATIFIDA; HYPERICUM ERECTUM FLOWERING TOP; LACTOBACILLUS REUTERI; CERAMIDE NP; MANGANESE PIDOLATE; BUTYLENE GLYCOL; BIOSACCHARIDE GUM-4; LEVOMENOL; ALLANTOIN; PHYTOSTERYL/OCTYLDODECYL LAUROYL GLUTAMATE; LAURYL BETAINE; CETYL STEARATE; ISOSTEARYL ISOSTEARATE; ALUMINUM HYDROXIDE; ASCORBYL GLUCOSIDE; DECYL ISOSTEARATE; POLYQUATERNIUM-51 (2-METHACRYLOYLOXYETHYL PHOSPHORYLCHOLINE/N-BUTYL METHACRYLATE; 3:7); HYALURONATE SODIUM; MICA; CARBOXYMETHYLCELLULOSE SODIUM, UNSPECIFIED; SILICON DIOXIDE; SODIUM PYRROLIDONE CARBOXYLATE; COCOYL CAPRYLOCAPRATE; DECYL GLUCOSIDE; POTASSIUM CETYL PHOSPHATE; CETYL ALCOHOL; ISOHEXADECANE; CAPRYLYL GLYCOL; HEXYLENE GLYCOL; SORBITAN MONOOLEATE; 1,2-HEXANEDIOL; SORBITAN SESQUIISOSTEARATE; SODIUM METHYL STEAROYL TAURATE; VINYLPYRROLIDONE/EICOSENE COPOLYMER; AMMONIUM ACRYLOYLDIMETHYLTAURATE, DIMETHYLACRYLAMIDE, LAURYL METHACRYLATE AND LAURETH-4 METHACRYLATE COPOLYMER, TRIMETHYLOLPROPANE TRIACRYLATE CROSSLINKED (45000 MPA.S); TERT-BUTYL ALCOHOL; POLYSORBATE 80; EDETATE DISODIUM; DIMETHICONE/VINYL DIMETHICONE CROSSPOLYMER (SOFT PARTICLE); SODIUM PHOSPHATE, DIBASIC, ANHYDROUS; ISOSTEARIC ACID; SODIUM CITRATE, UNSPECIFIED FORM; HYDROGEN DIMETHICONE (13 CST); SODIUM ACRYLATE/SODIUM ACRYLOYLDIMETHYLTAURATE COPOLYMER (4000000 MW); STEARIC ACID; CITRIC ACID MONOHYDRATE; TRIETHOXYCAPRYLYLSILANE; .ALPHA.-TOCOPHEROL; STANNIC OXIDE; ALCOHOL; LIMONENE, (+/-)-; LINALOOL, (+/-)-; .ALPHA.-HEXYLCINNAMALDEHYDE; SODIUM BENZOATE; PHENOXYETHANOL; FERRIC OXIDE RED; FERRIC OXIDE YELLOW; FERROSOFERRIC OXIDE

bareMinerals Complexion Rescue Defense Radiant Protective Veil Broad Spectrum SPF 30
Soft Radiance

Drug Facts

ACTIVE INGREDIENT

Active ingredients | Purpose
Titanium dioxide 3.28% | Sunscreen
Zinc oxide 12.48% | Sunscreen

Uses

- helps prevent sunburn
- if used as directed with other sun protection measures (see Directions), decreases the risk of skin cancer and early skin aging caused by the sun.

Warnings

For external use only

Do not use on damaged or broken skin.

When using this product keep out of eyes. Rinse with water to remove.

Stop use and ask a doctor if rash occurs.

Keep out of reach of children. If swallowed, get medical help or contact a Poison Control Center right away.

Directions

- For sunscreen use:
  - apply liberally 15 minutes before sun exposure
  - use a water resistant sunscreen if swimming or sweating
  - reapply at least every 2 hours
- Sun Protection Measures. Spending time in the sun increases your risk of skin cancer and early skin aging. To decrease this risk, regularly use a sunscreen with a broad spectrum SPF of 15 or higher and other sun protection measures including:
  - limit time in the sun, especially from 10 a.m. - 2 p.m.
  - wear long-sleeved shirts, pants, hats and sunglasses.
- children under 6 months: Ask a doctor

Other Information

Protect the product in this container from excessive heat and direct sun.

Inactive ingredients

water, c9-12 alkane, dimethicone, propanediol, glycerin, PEG-32, PEG-6, polyglyceryl-4 laurate/succinate, polysorbate 60, camellia japonica flower extract, bupleurum falcatum root extract, undaria pinnatifida extract, hypericum erectum flower/leaf/stem extract, moringa oleifera seed extract, theobroma cacao (cocoa) seed extract, lactobacillus ferment, ceramide np, manganese pca, butylene glycol, succinoglycan, biosaccharide gum-4, bisabolol, allantoin, phytosteryl/octyldodecyl, lauroyl glutamate, aminopropyl dimethicone, lauryl betaine, cetyl stearate, isostearyl isostearate, aluminum hydroxide, decyl isostearate, polyquaternium-51, sodium hyaluronate, ascorbyl glucoside, mica, cellulose gum, silica, sodium pca, coco-caprylate/caprate, decyl glucoside, potassium cetyl phosphate, cetyl alcohol, isohexadecane, caprylyl glycol, hexylene glycol, sorbitan oleate, 1,2-hexanediol, sorbitan sesquiisostearate, sodium methyl stearoyl taurate, vp/eicosene copolymer, polyacrylate crosspolymer-6, t-butyl alcohol, polysorbate 80, disodium edta, dimethylacrylamide/sodium acryloyldimethyltaurate crosspolymer, polysilicone-11, disodium phosphate, isostearic acid, sodium citrate, hydrogen dimethicone, sodium acrylate/sodium acryloyldimethyl taurate copolymer, stearic acid, citric acid, triethoxycaprylylsilane, tocopherol, tin oxide, alcohol, fragrance, limonene, linalool, hexyl cinnamal, sodium benzoate, phenoxyethanol. may contain: titanium dioxide, iron oxides.

Questions or comments?

Call toll free 1-888-795-4747

PRINCIPAL DISPLAY PANEL - 50 ml Tube Carton

bareMinerals

COMPLEXION
RESCUE
DEFENSE

RADIANT
PROTECTIVE VEIL

Broad Spectrum SPF 30
Sunscreen

50 ml/1.7 fl. oz.